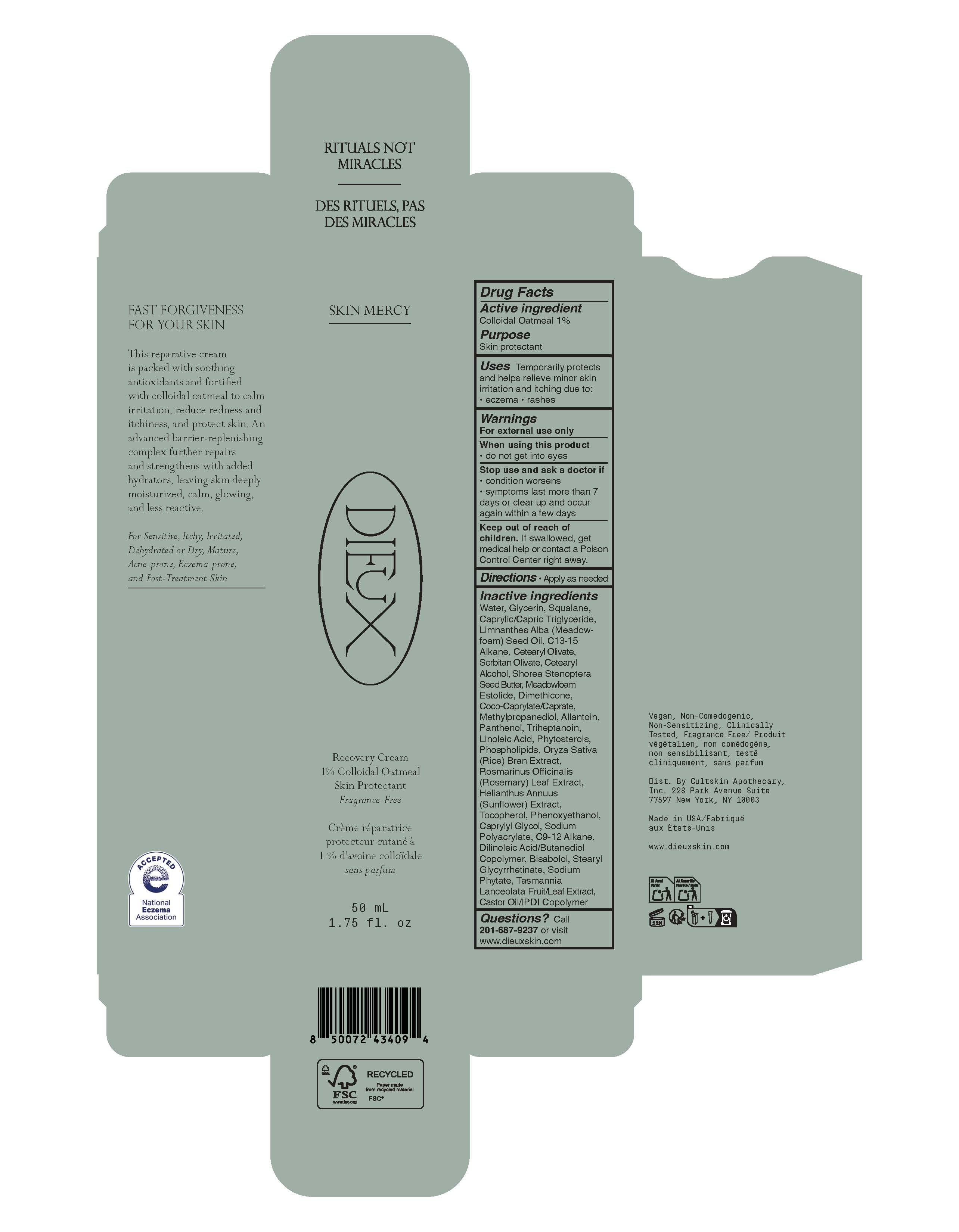 DRUG LABEL: Skin Mercy Recovery Cream
NDC: 80921-002 | Form: CREAM
Manufacturer: Cultskin Apothecary, Inc.
Category: otc | Type: HUMAN OTC DRUG LABEL
Date: 20260225

ACTIVE INGREDIENTS: OATMEAL 1 g/100 mL
INACTIVE INGREDIENTS: COCO-CAPRYLATE/CAPRATE; C9-12 ALKANE; DIMETHICONE; METHYLPROPANEDIOL; CETEARYL ALCOHOL; CAPRYLYL GLYCOL; STEARYL GLYCYRRHETINATE; ROSEMARY; TOCOPHEROL; CAPRYLIC/CAPRIC TRIGLYCERIDE; SORBITAN OLIVATE; HELIANTHUS ANNUUS FLOWERING TOP; WATER; LINOLEIC ACID; LIMNANTHES ALBA (MEADOWFOAM) SEED OIL; PANTHENOL; GLYCERIN; SQUALANE; DILINOLEIC ACID/BUTANEDIOL COPOLYMER; CETEARYL OLIVATE; CASTOR OIL/IPDI COPOLYMER; SODIUM PHYTATE; TASMANNIA LANCEOLATA WHOLE; ORYZA SATIVA (RICE) BRAN; TRIHEPTANOIN; MEADOWFOAM ESTOLIDE; C13-15 ALKANE; BISABOLOL; SHOREA STENOPTERA SEED BUTTER; ALLANTOIN; SODIUM POLYACRYLATE (2500000 MW); PHENOXYETHANOL

Drug Facts

Active ingredient

Colloidal Oatmeal 1%

Purpose

Skin protectant

Uses

Temporarily protects and helps relieve minor skin irritation and itching due to:

- eczema
- rashes

Warnings

For external use only

When using this product

- do not get into eyes

Stop use and ask a doctor if

- condition worsens
- symptoms last more than 7 days or clear up and occur again within a few days

Keep out of reach of children. If swallowed, get medical help or contact a Posion Control Center right away.

Directions

- Apply as needed

Inactive ingredients

Water, Glycerin, Squalane, Caprylic/Capric Triglyceride, Limnanthes Alba (Meadowfoam) Seed Oil, C13-15 Alkane, Cetearyl Olivate, Sorbitan Olivate, Cetearyl Alcohol, Shorea Stenoptera Seed Butter, Meadowfoam Estolide, Dimethicone, Coco-Caprylate/Caprate, Methylpropanediol, Allantoin, Panthenol, Triheptanoin, Linoleic Acid, Phytosterols, Phospholipids, Oryza Sativa (Rice) Bran Extract, Rosmarinus Officinalis (Rosemary) Leaf Extract, Helianthus Annuus (Sunflower) Extract, Tocopherol, Phenoxyethanol, Caprylyl Glycol, Sodium Polyacrylate, C9-12 Alkane, Dilinoleic Acid/Butanediol Copolymer, Bisabolol, Stearyl Glycyrrhetinate, Sodium Phytate, Tasmannia Lanceolata Fruit/Leaf Extract, Castor Oil/IPDI Copolymer

Questions?

Call 201-687-9237 or visit www.dieuxskin.com

Principal Display Panel - 50 mL Tube

SKIN MERCY

DIEUX

Recovery Cream
1% Colloidal Oatmeeal
Skin Protectant
Fragrance-Free

Crème réparatrice
protecteur cutané à
1% d’avoine colloïdale
sans parfum

50 mL
1.75 fl. oz.